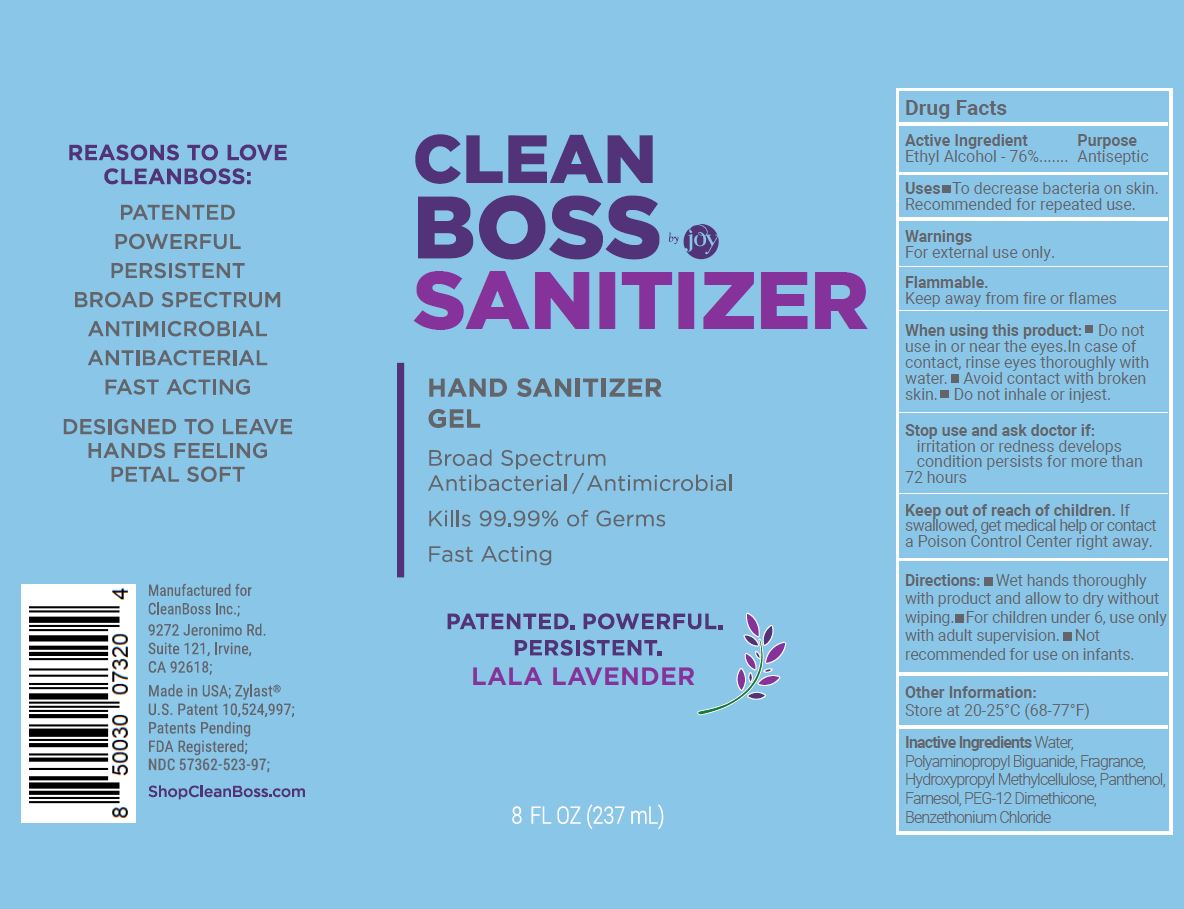 DRUG LABEL: CleanBoss Hand Sanitizer
NDC: 57362-523 | Form: GEL
Manufacturer: Innovative Biodefense, Inc
Category: otc | Type: HUMAN OTC DRUG LABEL
Date: 20251002

ACTIVE INGREDIENTS: ALCOHOL 76 mL/100 mL
INACTIVE INGREDIENTS: WATER

CleanBoss
Lala Lavender
Hand Sanitizer Gel

ACTIVE INGREDIENT

Ethyl Alcohol - 76 %

PURPOSE

Antiseptic

INDICATIONS AND USAGE

To decrease bacteria on skin. Recommended for repeated use.

WARNINGS

For external use only.

Flammable.

Keep away from fire or flames.

- Do not use in or near the eyes. In case of contact, rinse eyes thoroughly with water.
- avoid contact with broken skin.
- do not inhale or ingest.

STOP USE

- irritation or redness develops
- condition persist for more than 72 hours.

Keep out of reach of children. If swallowed, get medical help or contact a Poison Control Center right away.

DOSAGE AND ADMINISTRATION

- Wet hands thoroughly with product and allow to dry without wiping.
- For children under 6, use only with adult supervision.
- Not recommended for use on infants.

OTHER SAFETY INFORMATION

Store at 20-25ºC (68-77ºF)

INACTIVE INGREDIENT

Benzethonium Chloride, Farnesol, Fragrance, Hydroxypropyl Methylcellulose, Panthenol, PEG-12 Dimethicone, Polyaminopropyl Biguanide, Water.